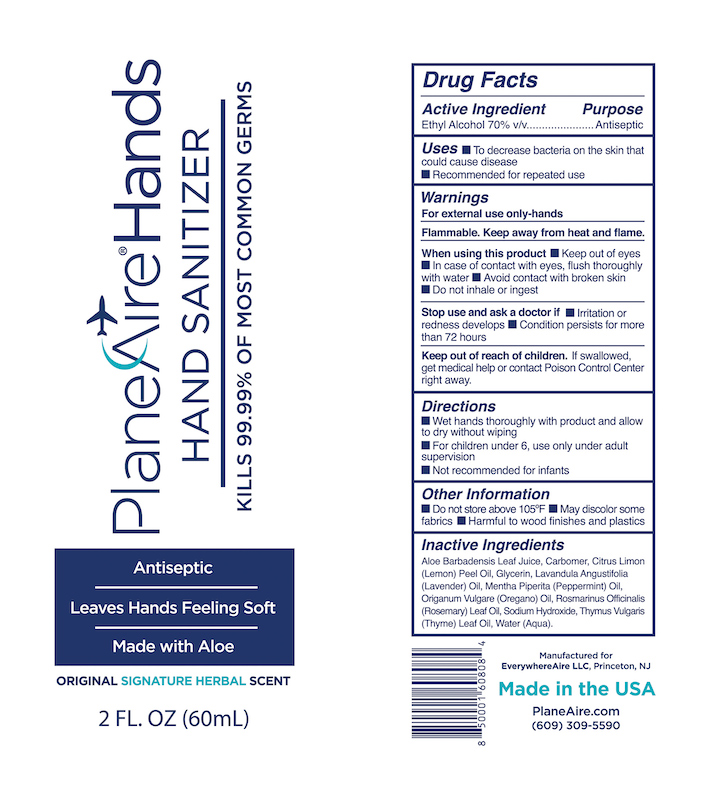 DRUG LABEL: PlaneAireHands hand sanitizer
NDC: 80335-102 | Form: GEL
Manufacturer: EverywhereAire LLC
Category: otc | Type: HUMAN OTC DRUG LABEL
Date: 20211008

ACTIVE INGREDIENTS: ALCOHOL 70 mL/100 mL
INACTIVE INGREDIENTS: THYMUS VULGARIS LEAF; OREGANO LEAF OIL; LAVENDER OIL; PEPPERMINT OIL; SODIUM HYDROXIDE; GLYCERIN; WATER; ROSEMARY OIL; CARBOMER 980; ALOE VERA LEAF POLYSACCHARIDES; LEMON OIL

PlaneAireHands gel Signature Herbal

This is a hand sanitizer

Active Ingredient(s)

Ethyl Alcohol 70% v/v. Purpose: Antiseptic

Purpose

Antiseptic

Use

To decrease bacteria on skin that could cause disease. Recommended for repeated use.

Warnings

For external use only.- hands. Flammable. Keep away from heat or flame

Do not use

- Not recommended for infants
- on open skin wounds

When using this product keep out of eyes. In case of contact with eyes, fllush eyes thoroughly with water.
(See Stop use section: Stop use and ask a doctor if irritation or rash occurs.)

Avoid contact with briken skin. Do not inhale or ingest.
Keep out of reach of children. If swallowed, get medical help or contact a Poison Control Center right away.

Stop use and ask a doctor if irritation or rash occurs. These may be signs of a serious condition.

Keep out of reach of children. If swallowed, get medical help or contact Poison Control Center right away.

Directions

- Wet hands thoroughly with product and allow to dry without wiping
- For children under 6, use only under adult supervision
- Not recommended for infants

Other information

- Do not store above 105F
- May discolor some fabrics
- Harmful to wood finishes and plastics

Inactive ingredients

glycerin, purified water, aloe vera leaf, carbomer 980, lemon oil, lavender oil, peppermint oil, oregano oil, rosemary oil, sodium hydroxide, thyme oil

RECENT MAJOR CHANGES

Indications and Usage

To decrease bacteria on skin that could cause diease. Recommended for repeated use.

Dosage and Administration

Wet hands thoroughly with product and allow to dry without wiping
For children under 6, use only under adult supervision
Not recommended for infants

Package Label - Principal Display Panel

60 mL NDC: 80335-102-02